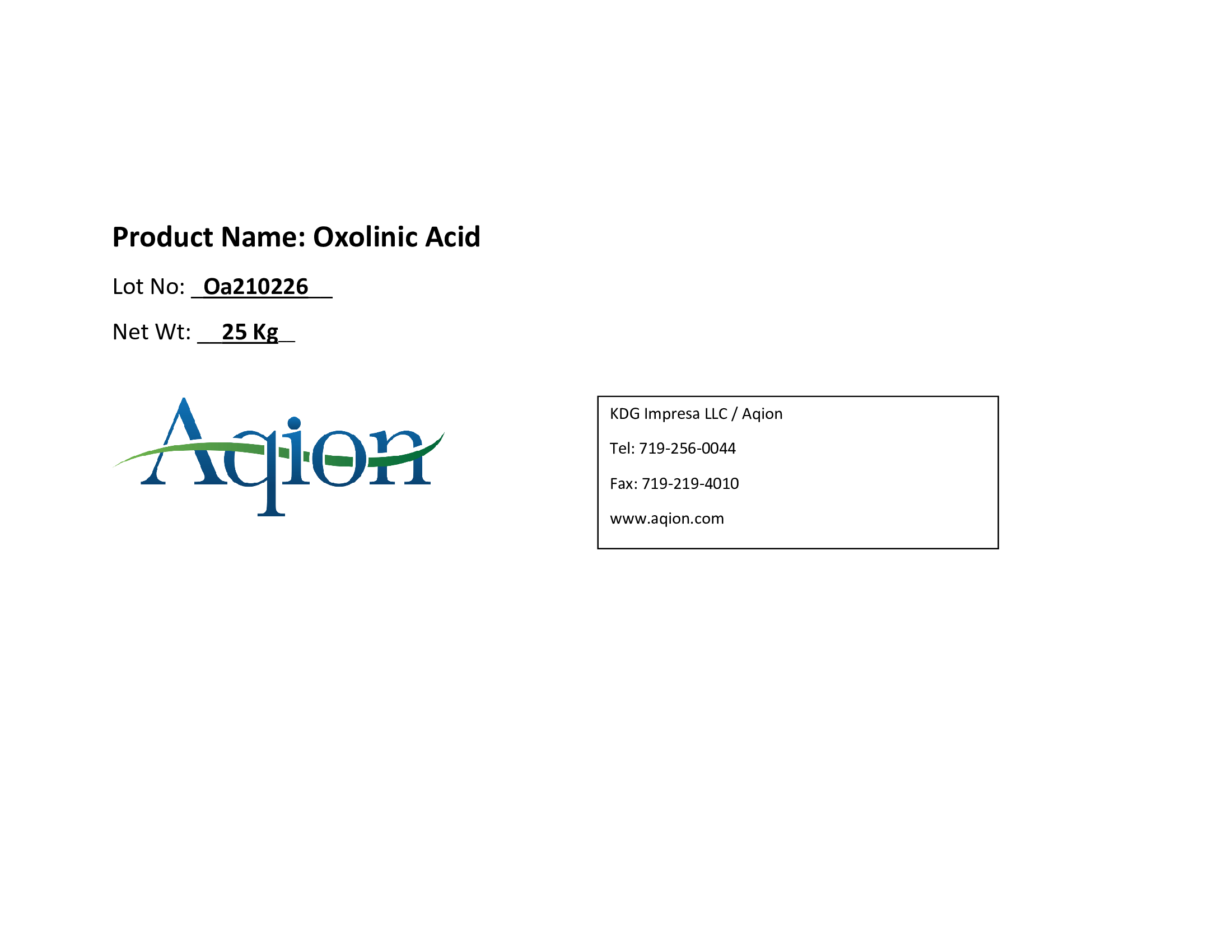 DRUG LABEL: Oxolinic Acid
NDC: 43457-536 | Form: POWDER
Manufacturer: KDG Impresa LLC, Aqion
Category: other | Type: BULK INGREDIENT - ANIMAL DRUG
Date: 20220221

ACTIVE INGREDIENTS: OXOLINIC ACID 1 kg/1 kg

Oxolinic Acid